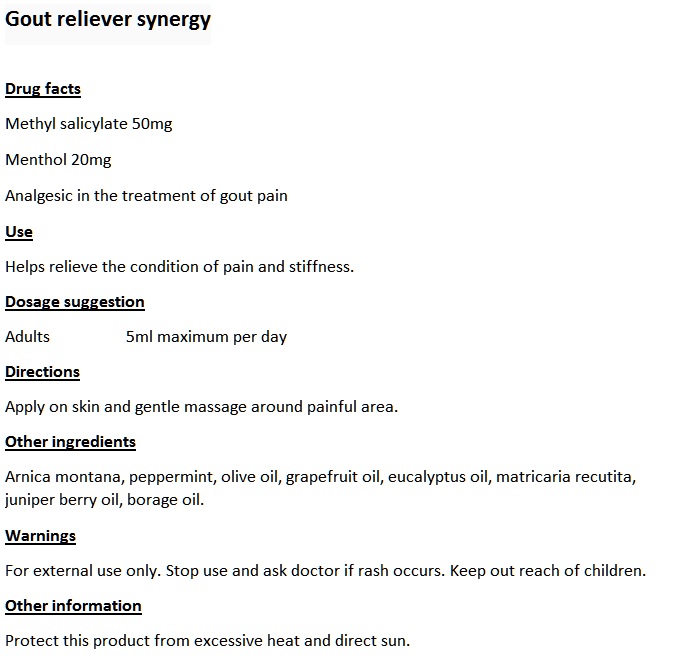 DRUG LABEL: Gout Reliever Synergy
NDC: 70470-1113 | Form: OIL
Manufacturer: PHYTOPIA CO., LTD.
Category: otc | Type: HUMAN OTC DRUG LABEL
Date: 20161024

ACTIVE INGREDIENTS: MENTHOL 20 mg/500 mg
INACTIVE INGREDIENTS: JUNIPER BERRY OIL; MATRICARIA RECUTITA; ARNICA MONTANA; BORAGE OIL; GAULTHERIA PROCUMBENS LEAF; PEPPERMINT OIL; GRAPEFRUIT OIL; EUCALYPTUS OIL; OLIVE OIL

Drug facts

Methyl salicylate 50mg

Menthol 20mg

Analgesic in the treatment of gout pain. Helps relieve the condition of pain and stiffness.

Drug facts

Methyl salicylate 50mg

Menthol 20mg

Analgesic in the treatment of gout pain. Helps relieve the condition of pain and stiffness.

Dosage and Usage

Adults 5ml maximum per day

Apply on skin and gentle massage around painful area.

Dosage and Usage

Adults 5ml maximum per day

Apply on skin and gentle massage around painful area.

INACTIVE INGREDIENT

Other ingredients

Arnica montana, peppermint, olive oil, grapefruit oil, eucalyptus oil, matricaria recutita, juniper berry oil, borage oil

Warnings

For external use only. Stop use and ask doctor if rash occurs. Keep out reach of children. Protect this product from excessive heat and direct sun.

Warnings

For external use only. Stop use and ask doctor if rash occurs. Keep out reach of children. Protect this product from excessive heat and direct sun.

Warnings

For external use only. Stop use and ask doctor if rash occurs. Keep out reach of children. Protect this product from excessive heat and direct sun.